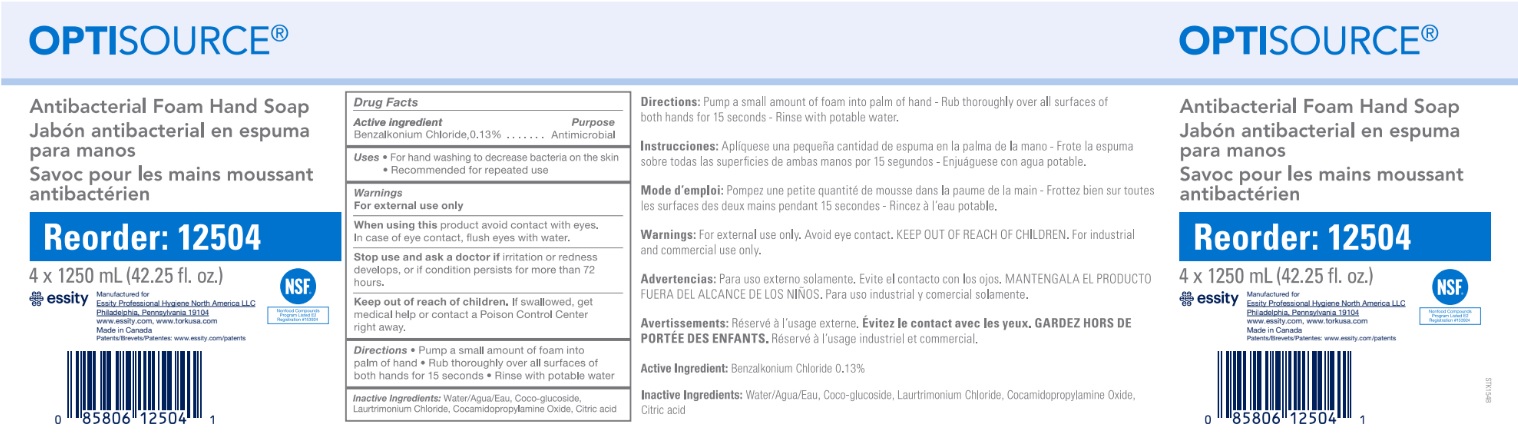 DRUG LABEL: OPTISOURCE Antibacterial Foam Hand
NDC: 64646-001 | Form: SOAP
Manufacturer: Charlotte Products Ltd.
Category: otc | Type: HUMAN OTC DRUG LABEL
Date: 20191204

ACTIVE INGREDIENTS: BENZALKONIUM CHLORIDE 1.3 mg/1 mL
INACTIVE INGREDIENTS: WATER; ANHYDROUS CITRIC ACID; COCAMIDOPROPYLAMINE OXIDE; LAURTRIMONIUM CHLORIDE; COCO GLUCOSIDE

Active ingredient

Benzalkonium Chloride 0.13%

Purpose

Antimicrobial

Uses

- For hand washing to decrease bacteria on the skin
- Recommended for repeated use

Warnings

For external use only

When using

this product avoid contact with eyes. In case of eye contact, flush eyes with water.

Stop using and ask doctor if

irritation or redness develops, or if condition persists for more than 72 hours.

Keep out of reach of children.

If swallowed, get medical help or contact a Poison Control Center right away.

Directions

- Pump a small amount of foam into palm of hand
- Rub thoroughly over all surfaces of both hands for 15 seconds
- Rinse with potable water

INACTIVE INGREDIENT

Inactive Ingredients Water/Agua/Eau, Coco-glucoside, Laurtrimonium Chloride, Cocamidopropylamine Oxide, Citric acid